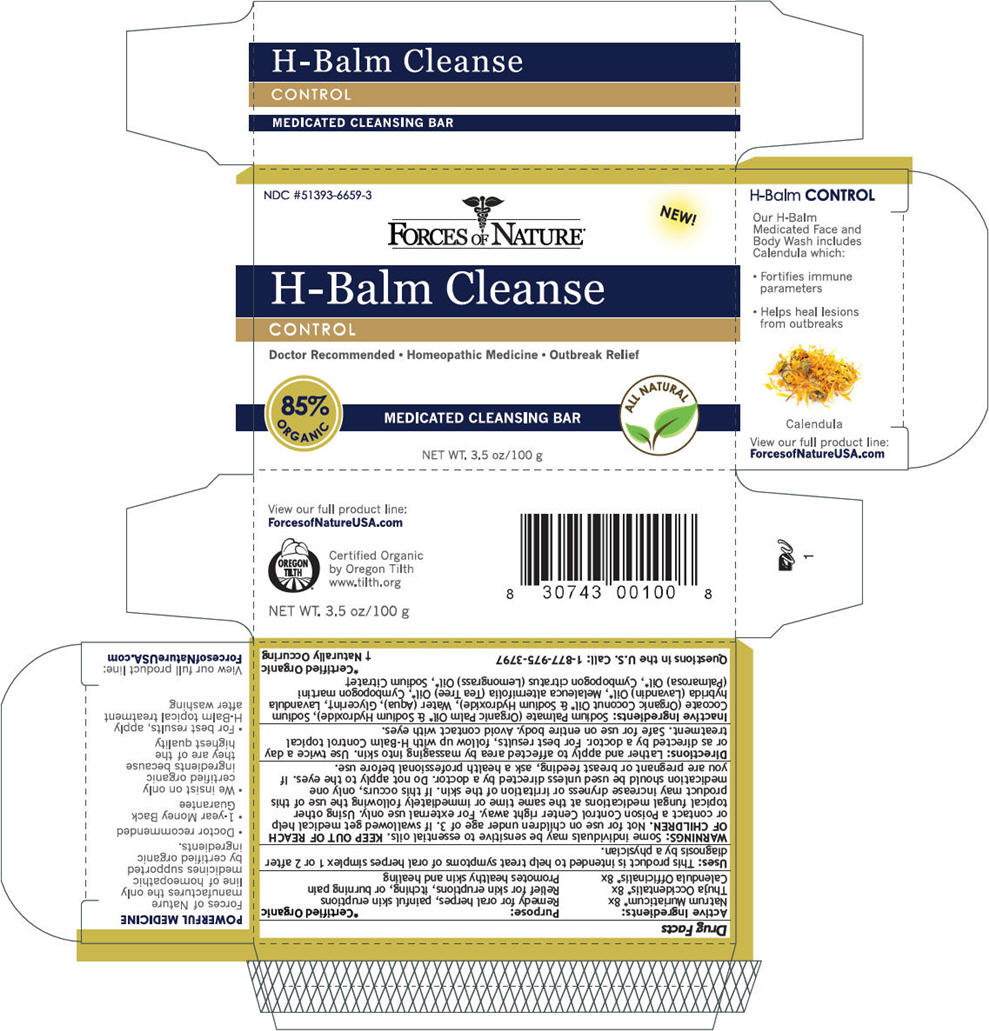 DRUG LABEL: H-Balm Cleanse
NDC: 51393-6659 | Form: SOAP
Manufacturer: Forces of Nature
Category: homeopathic | Type: HUMAN OTC DRUG LABEL
Date: 20131031

ACTIVE INGREDIENTS: Sodium Chloride 8 [hp_X]/100 g; Thuja Occidentalis Bark 8 [hp_X]/100 g; Calendula Officinalis Flowering Top 8 [hp_X]/100 g
INACTIVE INGREDIENTS: Sodium Palmate; Sodium Cocoate; Water; Glycerin; Lavandin Oil; Tea Tree Oil; Palmarosa Oil; West Indian Lemongrass Oil; Sodium Citrate

H-Balm Cleanse

Drug Facts

ACTIVE INGREDIENT

Active Ingredients: | Purpose:
Natrum Muriaticum [Certified Organic] 8x | Remedy for oral herpes, painful skin eruptions
Thuja Occidentalis 8x | Relief for skin eruptions, itching, or burning pain
Calendula Officinalis 8x | Promotes healthy skin and healing

Uses

This product is intended to help treat symptoms of oral herpes simplex 1 or 2 after diagnosis by a physician.

WARNINGS

Some individuals may be sensitive to essential oils.

KEEP OUT OF REACH OF CHILDREN. Not for use on children under age of 3. If swallowed get medical help or contact a Poison Control Center right away.

WHEN USING

For external use only. Using other topical fungal medications at the same time or immediately following the use of this product may increase dryness or irritation of the skin. If this occurs, only one medication should be used unless directed by a doctor. Do not apply to the eyes.

PREGNANCY OR BREAST FEEDING

If you are pregnant or breast feeding, ask a health professional before use.

Directions

Lather and apply to affected area by massaging into skin. Use twice a day or as directed by a doctor. For best results, follow up with H-Balm Control topical treatment. Safe for use on entire body. Avoid contact with eyes.

Inactive Ingredients

Sodium Palmate (Organic Palm Oil [Certified Organic] & Sodium Hydroxide), Sodium Cocoate (Organic Coconut Oil & Sodium Hydroxide), Water (Aqua), Glycerin [Naturally Occuring] , Lavandula hybrida (Lavandin) Oil, Melaleuca alternifolia (Tea Tree) Oil, Cymbopogon martini (Palmarosa) Oil, Cymbopogon citratus (Lemongrass) Oil, Sodium Citrate

Questions in the U.S. Call

1-877-975-3797

PRINCIPAL DISPLAY PANEL - 100 g Box

NDC #51393-6659-3

NEW!

FORCES OF NATURE®

H-Balm Cleanse

CONTROL

Doctor Recommended • Homeopathic Medicine • Outbreak Relief

85%
ORGANIC

MEDICATED CLEANSING BAR

ALL NATURAL

NET WT. 3.5 oz/100 g